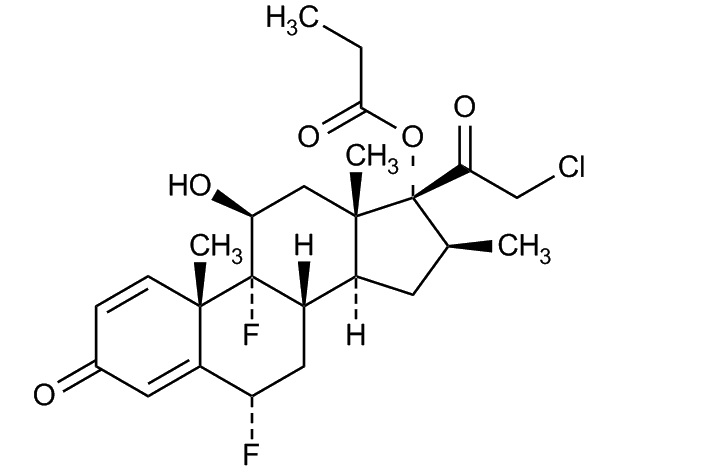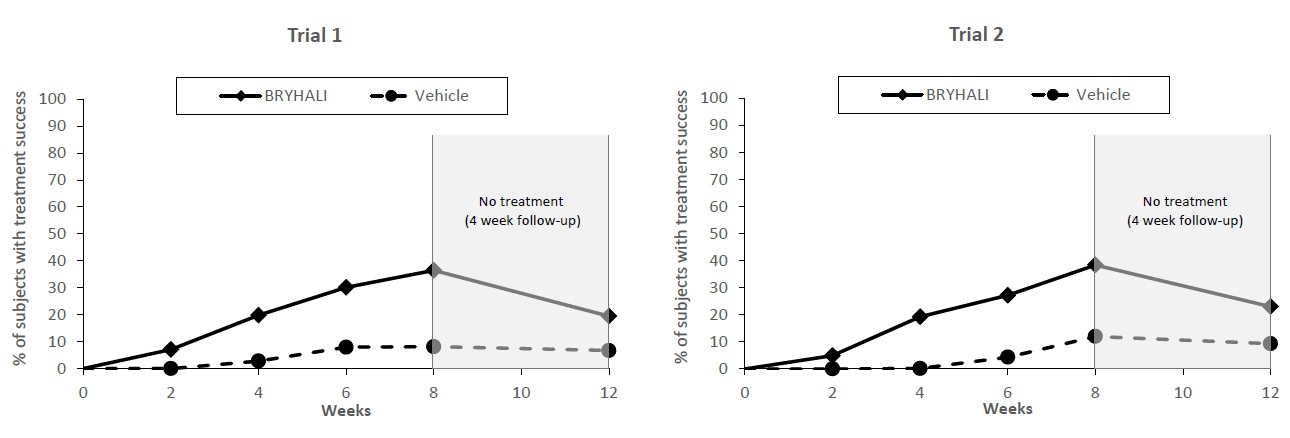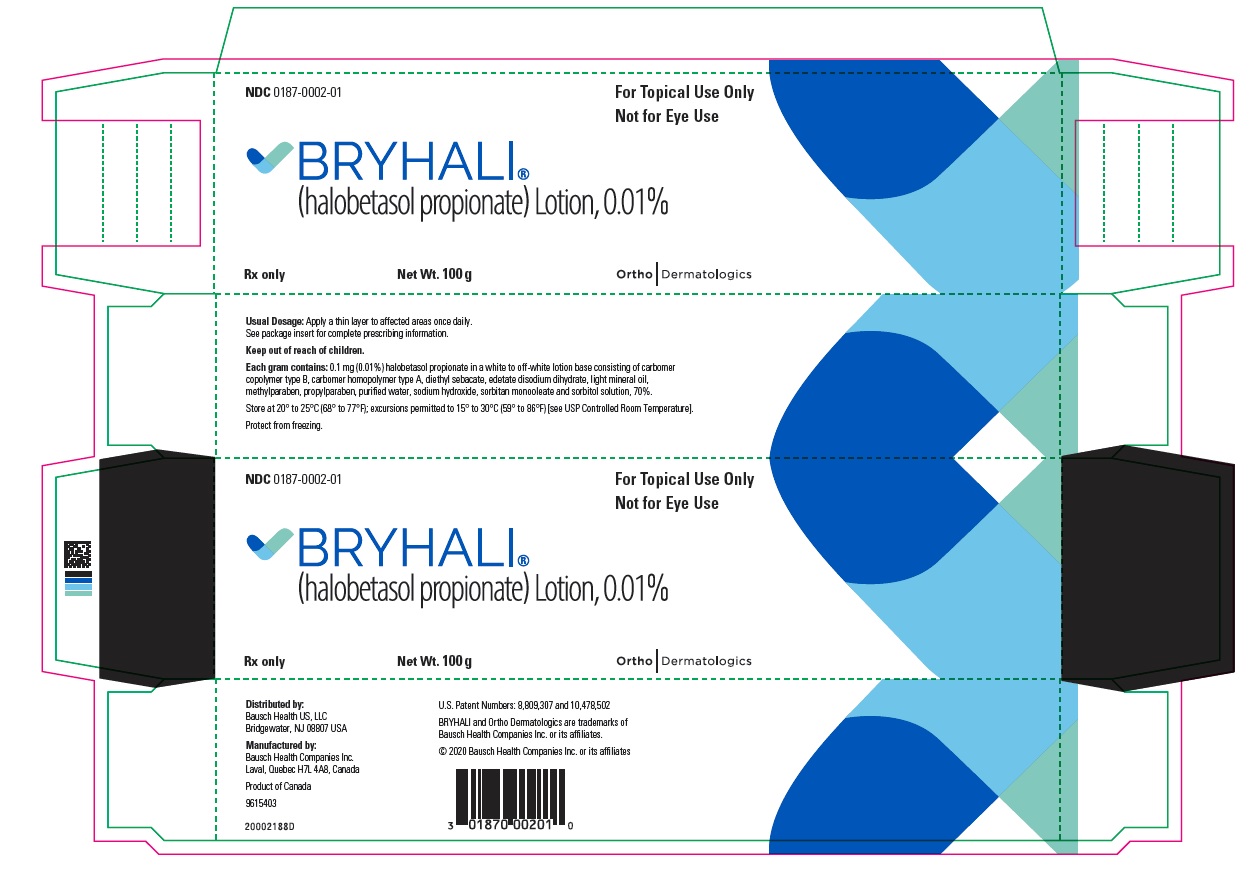 DRUG LABEL: Bryhali
NDC: 0187-0002 | Form: LOTION
Manufacturer: Bausch Health US, LLC
Category: prescription | Type: HUMAN PRESCRIPTION DRUG LABEL
Date: 20200601

ACTIVE INGREDIENTS: HALOBETASOL PROPIONATE 0.1 mg/1 g
INACTIVE INGREDIENTS: CARBOMER COPOLYMER TYPE B (ALLYL PENTAERYTHRITOL CROSSLINKED); CARBOMER HOMOPOLYMER TYPE A (ALLYL PENTAERYTHRITOL CROSSLINKED); DIETHYL SEBACATE; EDETATE DISODIUM; LIGHT MINERAL OIL; METHYLPARABEN; PROPYLPARABEN; WATER; SODIUM HYDROXIDE; SORBITAN MONOOLEATE; SORBITOL

HIGHLIGHTS OF PRESCRIBING INFORMATION

These highlights do not include all the information needed to use BRYHALI safely and effectively. See full prescribing information for BRYHALI.
BRYHALI® (halobetasol propionate) lotion, for topical use
Initial U.S. Approval: 1990

1 INDICATIONS AND USAGE

BRYHALI lotion is a corticosteroid indicated for the topical treatment of plaque psoriasis in adults. (1)

2 DOSAGE AND ADMINISTRATION

- Apply a thin layer of BRYHALI Lotion to the affected areas once daily. (2)
- Treatment beyond 8 weeks is not recommended. Discontinue treatment if control is achieved before 8 weeks. (2)
- Do not use with occlusive dressings unless directed by a physician. (2)
- Avoid use on the face, groin, or axillae. (2)
- Not for oral, ophthalmic, or intravaginal use. (2)

3 DOSAGE FORMS AND STRENGTHS

Lotion, 0.01% (3)

Each gram of BRYHALI Lotion contains 0.1 mg (0.01%) halobetasol propionate. (3)

4 CONTRAINDICATIONS

None (4).

5 WARNINGS AND PRECAUTIONS

- Reversible hypothalamic-pituitary-adrenal (HPA) axis suppression was observed and may occur with the potential for glucocorticosteroid insufficiency during or after treatment. (5.1)
- Systemic effects of topical corticosteroids may also include Cushing’s syndrome, hyperglycemia, and glucosuria. (5.1)
- Systemic absorption may require evaluation for HPA axis suppression. (5.1)
- Use of potent corticosteroids on large areas, for prolonged durations, under occlusive dressings, or on an altered skin barrier may increase systemic exposure. (5.1)
- Children may be more susceptible to systemic toxicity when treated with topical corticosteroids. (5.1, 8.4)
- Local adverse reactions may include atrophy, striae, telangiectasias, hypopigmentation, and allergic contact dermatitis. Some local adverse reactions may be irreversible. (5.2)
- Use of topical corticosteroids may increase the risk of posterior subcapsular cataracts and glaucoma. If visual symptoms occur, consider referral to an ophthalmologist for evaluation. (5.3)

6 ADVERSE REACTIONS

- The most common adverse reactions (≥1%) were upper respiratory tract infection, application site dermatitis and hyperglycemia. (6.1)

To report SUSPECTED ADVERSE REACTIONS, contact Bausch Health US, LLC at 1-800-321-4576 or FDA at 1-800-FDA-1088 or www.fda.gov/medwatch.

FULL PRESCRIBING INFORMATION

1 INDICATIONS AND USAGE

BRYHALI® (halobetasol propionate) lotion, 0.01% is indicated for the topical treatment of plaque psoriasis in adults.

2 DOSAGE AND ADMINISTRATION

Apply a thin layer of BRYHALI Lotion to affected areas once daily. Rub in gently. Wash hands after each application, unless BRYHALI Lotion is for treatment of the hands.

BRYHALI Lotion treatment beyond 8 weeks is not recommended, and the total dosage should not exceed approximately 50 g per week. Discontinue treatment if control is achieved before 8 weeks. Do not use with occlusive dressings unless directed by a physician.

BRYHALI Lotion should not be used on the face, groin, or in the axillae.

BRYHALI Lotion is not for oral, ophthalmic, or intravaginal use.

3 DOSAGE FORMS AND STRENGTHS

Lotion, 0.01%

Each gram of BRYHALI Lotion contains 0.1 mg (0.01%) halobetasol propionate in a white to off-white lotion.

4 CONTRAINDICATIONS

None.

5 WARNINGS AND PRECAUTIONS

5.1 Hypothalamic-Pituitary-Adrenal (HPA) Axis Suppression

BRYHALI Lotion has been shown to suppress the hypothalamic-pituitary-adrenal (HPA) axis.

Systemic effects of topical corticosteroids may include reversible HPA axis suppression with the potential for glucocorticosteroid insufficiency. This may occur during treatment or upon withdrawal of treatment with the topical corticosteroid.

The potential for hypothalamic-pituitary-adrenal (HPA) axis suppression with BRYHALI Lotion was evaluated in a study of 19 adult subjects with moderate to severe plaque psoriasis involving ≥20% of their body surface area (BSA). HPA axis suppression was reported for 1 (5.6%) subject at Week 4 and for 3 (15.8%) subjects at Week 8. All 3 subjects had normal HPA axis suppression test with discontinuation of treatment [see Clinical Pharmacology (12.2)].

Because of the potential for systemic absorption, use of topical corticosteroids, including BRYHALI Lotion, may require that patients be evaluated periodically for evidence of HPA axis suppression. Factors that predispose a patient using a topical corticosteroid to HPA axis suppression include the use of more potent corticosteroids, use over large surface areas, occlusive use, use on an altered skin barrier, concomitant use of multiple corticosteroid-containing products, liver failure, and young age. An adrenocorticotropic hormone (ACTH) stimulation test may be helpful in evaluating patients for HPA axis suppression.

If HPA axis suppression is documented, attempt to gradually withdraw the drug, reduce the frequency of application, or substitute a less potent steroid. Manifestations of adrenal insufficiency may require supplemental systemic corticosteroids. Recovery of HPA axis function is generally prompt and complete upon discontinuation of topical corticosteroids.

Systemic effects of topical corticosteroids may also include Cushing’s syndrome, hyperglycemia, and glucosuria. Use of more than one corticosteroid-containing product at the same time may increase the total systemic exposure to corticosteroids. Pediatric patients may be more susceptible than adults to systemic toxicity from the use of topical corticosteroids due to their larger surface-to-body-mass ratios [see Use in Specific Populations (8.4)].

5.2 Local Adverse Reactions

Local adverse reactions from topical corticosteroids may include atrophy, striae, telangiectasias, burning, itching, irritation, dryness, folliculitis, acneiform eruptions, hypopigmentation, perioral dermatitis, allergic contact dermatitis, secondary infection, and miliaria. These may be more likely with occlusive use, prolonged use, or use of higher potency corticosteroids, including BRYHALI Lotion. Some local adverse reactions may be irreversible.

5.3 Ophthalmic Adverse Reactions

Use of topical corticosteroids may increase the risk of posterior subcapsular cataracts and glaucoma. Cataracts and glaucoma have been reported in postmarketing experience with the use of topical corticosteroid products. Advise patients to report any visual symptoms and consider referral to an ophthalmologist for evaluation.

5.4 Concomitant Skin Infections

Use an appropriate antimicrobial agent if a skin infection is present or develops. If a favorable response does not occur promptly, discontinue use of BRYHALI Lotion until the infection has been adequately treated.

5.5 Allergic Contact Dermatitis

Allergic contact dermatitis with corticosteroids is usually diagnosed by observing failure to heal rather than noting a clinical exacerbation. Consider confirmation of a clinical diagnosis of allergic contact dermatitis by appropriate patch testing. Discontinue BRYHALI Lotion if allergic contact dermatitis occurs.

6 ADVERSE REACTIONS

6.1 Clinical Trials Experience

Because clinical trials are conducted under widely varying conditions, adverse reaction rates observed in the clinical trials of a drug cannot be directly compared to rates in the clinical trials of another drug and may not reflect the rates observed in clinical practice.

In randomized, double-blind, multicenter, vehicle-controlled clinical trials, 426 adults with plaque psoriasis were treated with BRYHALI Lotion and had post-baseline safety data. Subjects applied BRYHALI Lotion once daily for up to 8 weeks. Table 1 presents adverse reactions that occurred in at least 1% of subjects treated with BRYHALI Lotion and more frequently than in vehicle-treated subjects.

Table 1: Adverse Reactions Occurring in ≥1% of the Subjects Treated with BRYHALI Lotion through Week 8
 | BRYHALI Lotion; (N=284) | Vehicle Lotion; (N=142)
Adverse Reaction | % | %
Upper Respiratory Tract Infection | 2% | 1%
Application Site Dermatitis | 1% | 0
Hyperglycemia | 1% | 0

8 USE IN SPECIFIC POPULATIONS

8.1 Pregnancy

Risk Summary

There are no available data on BRYHALI Lotion use in pregnant women to inform a drug-associated risk of major birth defects, miscarriage, or adverse maternal or fetal outcomes.

In animal reproduction studies, increased malformations, including cleft palate and omphalocele, were observed after oral administration of halobetasol propionate during organogenesis to pregnant rats and rabbits. The available data do not support relevant comparisons of systemic halobetasol propionate exposures achieved in the animal studies to exposures observed in humans after topical use of BRYHALI Lotion.

The background risk of major birth defects and miscarriage for the indicated population is unknown. In the U.S. general population, the estimated background risk of major birth defects and miscarriage in clinically recognized pregnancies is 2 to 4% and 15 to 20%, respectively.

Data

Animal Data

Halobetasol propionate has been shown to cause malformations in rats and rabbits when given orally during organogenesis at doses of 0.04 to 0.1 mg/kg/day in rats and 0.01 mg/kg/day in rabbits. Halobetasol propionate was embryotoxic in rabbits but not in rats. Cleft palate was observed in both rats and rabbits. Omphalocele was seen in rats but not in rabbits.

8.2 Lactation

Risk Summary

There are no data on the presence of halobetasol propionate or its metabolites in human milk, the effects on the breastfed infant, or the effects on milk production after treatment with BRYHALI Lotion.

Systemically administered corticosteroids appear in human milk and could suppress growth, interfere with endogenous corticosteroid production, or cause other untoward effects. It is not known whether topical administration of corticosteroids could result in sufficient systemic absorption to produce detectable quantities in human milk.

The developmental and health benefits of breastfeeding should be considered along with the mother’s clinical need for BRYHALI Lotion and any potential adverse effects on the breastfed child from BRYHALI Lotion.

Clinical Considerations

Advise breastfeeding women not to apply BRYHALI Lotion directly to the nipple and areola to avoid direct infant exposure.

8.4 Pediatric Use

Safety and effectiveness of BRYHALI Lotion in pediatric patients under the age of 18 years have not been evaluated.

Because of higher skin-surface-area-to-body-mass ratios, pediatric patients are at a greater risk than adults of HPA axis suppression and Cushing’s syndrome when they are treated with topical corticosteroids. They are therefore also at greater risk of adrenal insufficiency during or after withdrawal of treatment. Adverse reactions including striae have been reported with use of topical corticosteroids in infants and children [see Warnings and Precautions (5.1)].

HPA axis suppression, Cushing’s syndrome, linear growth retardation, delayed weight gain, and intracranial hypertension have been reported in children receiving topical corticosteroids. Manifestations of adrenal suppression in children include low plasma cortisol levels and an absence of response to ACTH stimulation. Manifestations of intracranial hypertension include bulging fontanelles, headaches, and bilateral papilledema [see Warnings and Precautions (5.1)].

8.5 Geriatric Use

Of 284 subjects exposed to BRYHALI Lotion in clinical trials, 61 subjects were 65 years or older. Clinical trials of BRYHALI Lotion did not include sufficient numbers of subjects age 65 years and older to determine whether they respond differently from younger subjects.

11 DESCRIPTION

BRYHALI (halobetasol propionate) lotion contains a corticosteroid, halobetasol propionate, as the active ingredient in a white to off-white lotion formulation intended for topical use.

Halobetasol propionate is a synthetic corticosteroid. The chemical name for halobetasol propionate is 21-chloro-6α, 9-difluoro-11β, 17-dihydroxy-16β-methylpregna-1, 4-diene-3, 20 –dione, 17-propionate. Halobetasol propionate is a white to off-white crystalline powder with a molecular weight of 484.96 and a molecular formula of C25H31ClF2O5. It is practically insoluble in water and freely soluble in dichloromethane and in acetone. The structural formula for halobetasol propionate is represented below:

Each gram of BRYHALI Lotion contains 0.1 mg (0.01%) halobetasol propionate in a white to off-white lotion base consisting of carbomer copolymer type B, carbomer homopolymer type A, diethyl sebacate, edetate disodium dihydrate, light mineral oil, methylparaben, propylparaben, purified water, sodium hydroxide, sorbitan monooleate and sorbitol solution, 70%.

12 CLINICAL PHARMACOLOGY

12.1 Mechanism of Action

Corticosteroids play a role in cellular signaling, immune function, inflammation, and protein regulation; however, the precise mechanism of action in plaque psoriasis is unknown.

12.2 Pharmacodynamics

Vasoconstrictor Assay

A vasoconstrictor assay in healthy subjects with BRYHALI Lotion indicated that the formulation is in the potent to superpotent range of potency as compared to other topical corticosteroids. However, similar blanching scores do not necessarily imply therapeutic equivalence.

Hypothalamic-Pituitary-Adrenal (HPA) Axis Suppression

The potential for HPA axis suppression was evaluated in 19 adult subjects with moderate to severe plaque psoriasis with at least 20% BSA involved. An approximate dose of 7 g BRYHALI Lotion was applied once daily for 8 weeks. An abnormal HPA axis suppression test, as indicated by a 30-minute post-stimulation cortisol level ≤18 mcg/dL, was reported for 1 (5.6%) subject at Week 4 and for 3 (15.8%) subjects at Week 8. The subject suppressed at Week 4 was also suppressed at Week 8. These effects were reversible as recovery of HPA axis function was generally prompt with the discontinuation of treatment. [See Warnings and Precautions (5.1).]

12.3 Pharmacokinetics

The extent of percutaneous absorption of topical corticosteroids is determined by many factors, including the vehicle, the integrity of the epidermal barrier, and the use of occlusive dressings. Topical corticosteroids can be absorbed from normal intact skin. Inflammation and/or other disease processes in the skin may increase percutaneous absorption.

In an open-label, randomized, pharmacokinetic study, 23 subjects aged 18 years and older with moderate to severe plaque psoriasis applied approximately 7 grams of BRYHALI Lotion to a mean BSA of 27.7±11.3% once daily for 28 days. Systemic concentrations were at steady state by Day 14. Only 5 out of 20 subjects had one or more quantifiable systemic concentrations of halobetasol propionate on Day 14. The mean ± SD for maximum systemic concentration (Cmax) on Day 14 was 31.2±62.2 pg/mL. The mean area under the concentration versus time curve (AUC) could not be reliably estimated due to insufficient number of quantifiable timepoints.

13 NONCLINICAL TOXICOLOGY

13.1 Carcinogenesis, Mutagenesis, Impairment of Fertility

Long-term animal studies have not been performed to evaluate the carcinogenic potential of halobetasol propionate.

Halobetasol propionate was not genotoxic in the Ames assay, in the sister chromatid exchange test in Chinese hamster somatic cells, in chromosome aberration studies of germinal and somatic cells of rodents, or in a mammalian spot test. Positive mutagenicity effects were observed in a mouse lymphoma gene mutation assay in vitro and in a Chinese hamster micronucleus test.

Studies in rats following oral administration of halobetasol propionate at dose levels up to 0.05 mg/kg/day indicated no impairment of fertility or general reproductive performance.

14 CLINICAL STUDIES

BRYHALI Lotion was evaluated for the treatment of moderate to severe plaque psoriasis in two prospective, multicenter, randomized, double-blind clinical trials (Trial 1 [NCT02514577] and Trial 2 [NCT02515097]). These trials were conducted in 430 subjects 18 years of age and older with moderate to severe plaque psoriasis that covered a body surface area (BSA) between 3% and 12% excluding the face, scalp, palms, soles, axillae, and intertriginous areas. Disease severity was determined by a 5-grade Investigator’s Global Assessment (IGA). Subjects applied BRYHALI Lotion or vehicle to all affected areas once daily for up to 8 weeks. Subjects had a follow-up visit 4 weeks after the end of treatment (Week 12) where safety and efficacy were evaluated.

The primary efficacy endpoint was the proportion of subjects with treatment success at Week 8, where treatment success was defined as at least a 2-grade improvement from baseline in IGA score and an IGA score equating to “clear” or “almost clear”. Table 2 lists the primary efficacy results for Trials 1 and 2. The secondary efficacy endpoints evaluated treatment success sequentially at Weeks 12, 6, 4, and 2. Figure 1 shows the primary and secondary efficacy results over time.

Table 2: Primary Efficacy Results at Week 8 in Subjects with Moderate to Severe Plaque Psoriasis
 | Trial 1 |  | Trial 2
 | BRYHALI | Vehicle | BRYHALI | Vehicle
 | N=143 | N=74 | N=142 | N=71
IGA Treatment Success at Week 8 [Treatment success was defined as at least a 2-grade improvement from baseline in IGA score and an IGA score equating to “clear” or “almost clear”. Clear = no evidence of scaling, no evidence of erythema, no evidence of plaque elevation above normal skin level. Almost clear = some plaques with fine scales, faint pink/light red erythema on most plaques, slight or barely perceptible elevation of plaques above normal skin level.] | 37% | 8% | 38% | 12%

*The treatment difference at Week 2 in Trial 2 was not statistically significant.

16 HOW SUPPLIED/STORAGE AND HANDLING

BRYHALI (halobetasol propionate) lotion, 0.01% is a white to off-white lotion supplied in a white aluminum tube as follows:

- 60 g (NDC 0187-0002-60)
- 100 g (NDC 0187-0002-01)

Storage and Handling Conditions

Store at 20° to 25°C (68° to 77°F); excursions permitted to 15° to 30°C (59° to 86°F) [see USP Controlled Room Temperature]. Protect from freezing.

17 PATIENT COUNSELING INFORMATION

Advise the patient to read the FDA-approved patient labeling (Patient Information).

This information is intended to aid in the safe and effective use of this medication. It is not a disclosure of all administration instructions or all possible adverse or unintended effects.

Advise patients using BRYHALI Lotion of the following information and instructions:

Important Administration Instructions

Instruct patients to discontinue BRYHALI Lotion when psoriasis is controlled. Inform patients that BRYHALI Lotion is to be used as directed by the physician and should not be used for longer than the prescribed time period. Total dosage should not exceed 50 grams per week [see Dosage and Administration (2)].

Instruct patients to avoid bandaging, wrapping or otherwise occluding the treatment area(s), unless directed by physician. Advise patients to avoid use on the face, groin, or axillae [see Dosage and Administration (2)].

Inform patients that BRYHALI Lotion is for external use only. Advise patients that BRYHALI Lotion is not for oral, ophthalmic, or intravaginal use [see Dosage and Administration (2)].

Breastfeeding women should not apply BRYHALI Lotion directly to the nipple and areola to avoid directly exposing the infant [see Use in Specific Populations (8.2)].

Effects on Endocrine System

BRYHALI Lotion may cause HPA axis suppression. Advise patients that use of topical corticosteroids, including BRYHALI Lotion, may require periodic evaluation for HPA axis suppression. Topical corticosteroids may have other endocrine effects. Concomitant use of multiple corticosteroid-containing products may increase the total systemic exposure to topical corticosteroids [see Warnings and Precautions (5.1)].

Local Adverse Reactions

Inform patients that BRYHALI Lotion may cause local adverse reactions. These reactions may be more likely to occur with occlusive use or prolonged use of BRYHALI Lotion [see Warnings and Precautions (5.2)].

Distributed by:
Bausch Health US, LLC
Bridgewater, NJ 08807 USA

Manufactured by:
Bausch Health Companies Inc.
Laval, Quebec H7L 4A8, Canada

U.S. Patent Numbers: 8,809,307 and 10,478,502

BRYHALI is a trademark of Bausch Health Companies Inc. or its affiliates.

© 2020 Bausch Health Companies Inc. or its affiliates
9652104

TEAR HERE (Patient Information)

Patient Package Insert

PATIENT INFORMATION

BRYHALI® (bry-HAL-ee)

(halobetasol propionate) Lotion

Important: BRYHALI is for use on the skin only. Do not apply BRYHALI in your mouth, eyes, or vagina.

What is BRYHALI?

BRYHALI is a prescription corticosteroid medicine used on the skin (topical) to treat adults with plaque psoriasis.

It is not known if BRYHALI is safe and effective in children under 18 years of age.

Before using BRYHALI, tell your doctor about all of your medical conditions, including if you:

- have had irritation or other skin reaction to a steroid medicine in the past.
- have a skin infection. You may need medicine to treat the skin infection before using BRYHALI.
- have diabetes.
- have adrenal gland problems.
- have liver problems.
- are pregnant or plan to become pregnant. It is not known if BRYHALI will harm your unborn baby.
- are breastfeeding or plan to breastfeed. It is not known if BRYHALI passes into your breast milk. If you use BRYHALI and breastfeed, do not apply BRYHALI to your nipple or areola to avoid getting BRYHALI into your baby’s mouth.

Tell your doctor about all the medicines you take, including prescription and over-the-counter medicines, vitamins, and herbal supplements. Especially tell your doctor if you take other corticosteroids medicines by mouth, or injection, or use other products on your skin that contain corticosteroids.

How should I use BRYHALI?

- Use BRYHALI exactly as your doctor tells you to use it.
- Apply a thin layer of BRYHALI to the affected areas 1 time each day and rub in gently.
- You should not use more than 50 g of BRYHALI in 1 week.
- Do not bandage, wrap, or cover the treated skin area(s) unless your doctor tells you to.
- Avoid using BRYHALI on your face, groin, or underarms (armpits).
- Talk to your doctor if your skin does not improve after 8 weeks of treatment with BRYHALI.
- You should not use BRYHALI longer than 8 weeks unless your doctor tells you to.
- Wash your hands after using BRYHALI unless you are using the medicine to treat your hands.

What are the possible side effects of BRYHALI?

BRYHALI may cause serious side effects, including:

- BRYHALI can pass through your skin. Too much BRYHALI passing through your skin can cause adrenal glands to stop working.
- Cushing’s syndrome, a condition that happens when your body is exposed to too much of the hormone cortisol.
- High blood sugar (hyperglycemia).
- Skin reactions at the treated skin site. Tell your doctor if you get any skin reactions or skin infections.
- Vision problems. BRYHALI may increase your chance of developing cataract(s) and glaucoma. Tell your healthcare provider if you develop blurred vision or other vision problems during treatment with BRYHALI.
- Effects on growth and weight in children.

The most common side effects of BRYHALI include burning, stinging, itching, dryness (application site dermatitis), upper respiratory tract infection and high blood sugar (hyperglycemia).

These are not all the possible side effects of BRYHALI.

Call your doctor for medical advice about side effects. You may report side effects to FDA at 1-800-FDA-1088.

How should I store BRYHALI?

- Store BRYHALI at room temperature between 68° to 77°F (20° to 25°C).
- Protect from freezing.
Keep BRYHALI and all medicines out of the reach of children.

General information about the safe and effective use of BRYHALI.

Medicines are sometimes prescribed for purposes other than those listed in a Patient Information leaflet. Do not use BRYHALI for a condition for which it was not prescribed. Do not give BRYHALI to other people, even if they have the same condition you have. It may harm them. You can ask your pharmacist or doctor for information about BRYHALI that is written for health professionals.

What are the ingredients in BRYHALI?

Active ingredients: halobetasol propionate

Inactive ingredients: carbomer copolymer type B, carbomer homopolymer type A, diethyl sebacate, edetate disodium dihydrate, light mineral oil, methylparaben, propylparaben, purified water, sodium hydroxide, sorbitan monooleate and sorbitol solution, 70%.

Distributed by: Bausch Health US, LLC, Bridgewater, NJ 08807 USA
Manufactured by: Bausch Health Companies Inc., Laval, Quebec H7L 4A8, Canada

U.S. Patent Numbers: 8,809,307 and 10,478,502

BRYHALI is a trademark of Bausch Health Companies Inc. or its affiliates.

© 2020 Bausch Health Companies Inc. or its affiliates

For more information, go to www.bauschhealth.com or call 1-800-321-4576.
This Patient Information has been approved by the U.S. Food and Drug Administration.
9652104
Revised: 06/2020

PACKAGE/LABEL PRINCIPAL DISPLAY PANEL

NDC 0187-0002-01

For Topical Use Only
Not for Eye Use

BRYHALI®
(halobetasol propionate) Lotion, 0.01%

Rx only

Net Wt. 100 g

Ortho Dermatologics